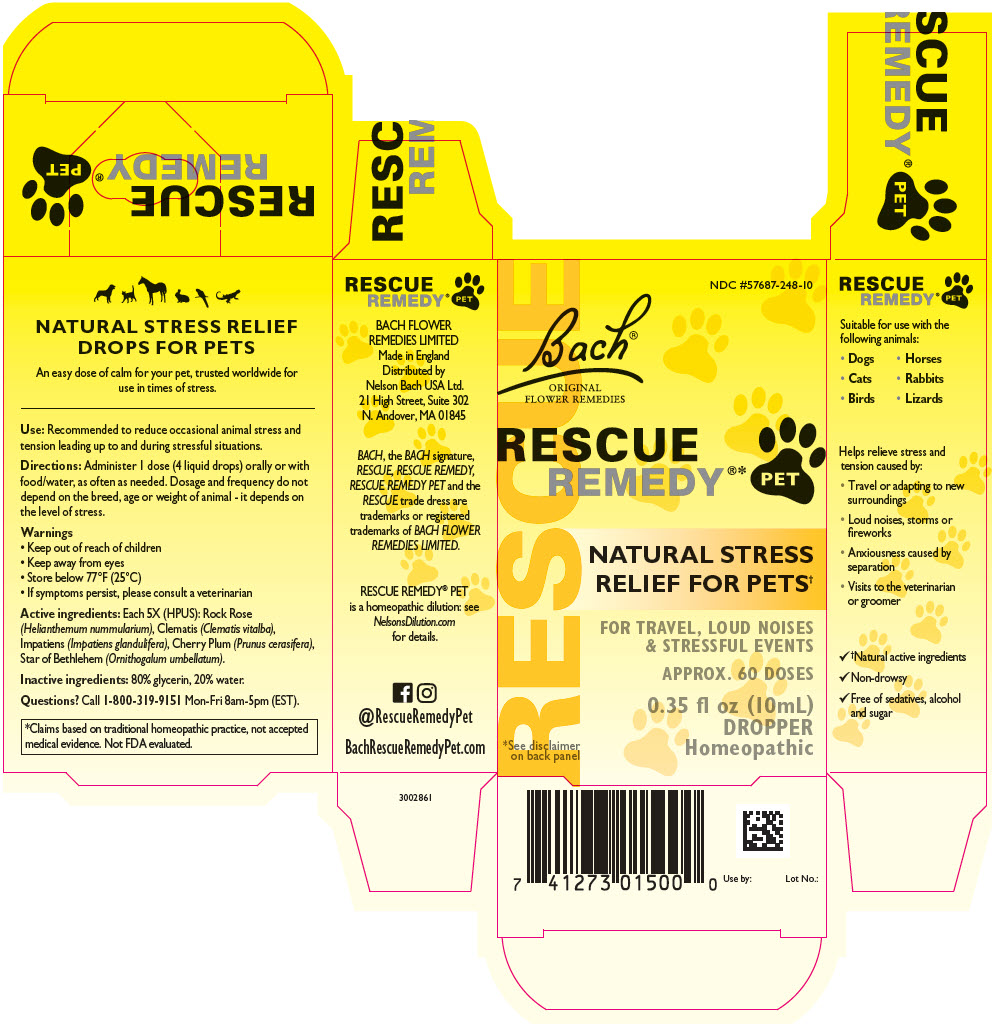 DRUG LABEL: Rescue Remedy 
NDC: 57687-248 | Form: TINCTURE
Manufacturer: Nelson Bach USA, Ltd.
Category: homeopathic | Type: OTC ANIMAL DRUG LABEL
Date: 20200902

ACTIVE INGREDIENTS: HELIANTHEMUM NUMMULARIUM FLOWER 5 [hp_X]/1 mL; CLEMATIS VITALBA FLOWER 5 [hp_X]/1 mL; IMPATIENS GLANDULIFERA FLOWER 5 [hp_X]/1 mL; PRUNUS CERASIFERA FLOWER 5 [hp_X]/1 mL; ORNITHOGALUM UMBELLATUM WHOLE 5 [hp_X]/1 mL
INACTIVE INGREDIENTS: GLYCERIN; WATER

RESCUE REMEDY® PET

NATURAL STRESS RELIEF DROPS FOR PETS

An easy dose of calm for your pet, trusted worldwide for use in times of stress.

VETERINARY INDICATIONS

Use: Recommended to reduce occasional animal stress and tension leading up to and during stressful situations.

DOSAGE AND ADMINISTRATION

Directions: Administer 1 dose (4 liquid drops) orally or with food/water, as often as needed. Dosage and frequency do not depend on the breed, age or weight of animal - it depends on the level of stress.

Warnings

- Keep out of reach of children
- Keep away from eyes
- Store below 77°F (25°C)
- If symptoms persist, please consult a veterinarian

DESCRIPTION

Active ingredients: Each 5X (HPUS): Rock Rose (Helianthemum nummularium), Clematis (Clematis vitalba), Impatiens (Impatiens glandulifera), Cherry Plum (Prunus cerasifera), Star of Bethlehem (Ornithogalum umbellatum).

Inactive ingredients: 80% glycerin, 20% water.

Questions? Call 1-800-319-9151 Mon-Fri 8am-5pm (EST).

*Claims based on traditional homeopathic practice, not accepted medical evidence. Not FDA evaluated.

PRINCIPAL DISPLAY PANEL - 10 mL Bottle Carton

RESCUE

NDC #57687-248-10

Bach®
ORIGINAL
FLOWER REMEDIES

RESCUE
REMEDY®*
PET

NATURAL STRESS
RELIEF FOR PETS†

FOR TRAVEL, LOUD NOISES
& STRESSFUL EVENTS

APPROX. 60 DOSES

0.35 fl oz (10mL)
DROPPER
Homeopathic

*See disclaimer
on back panel